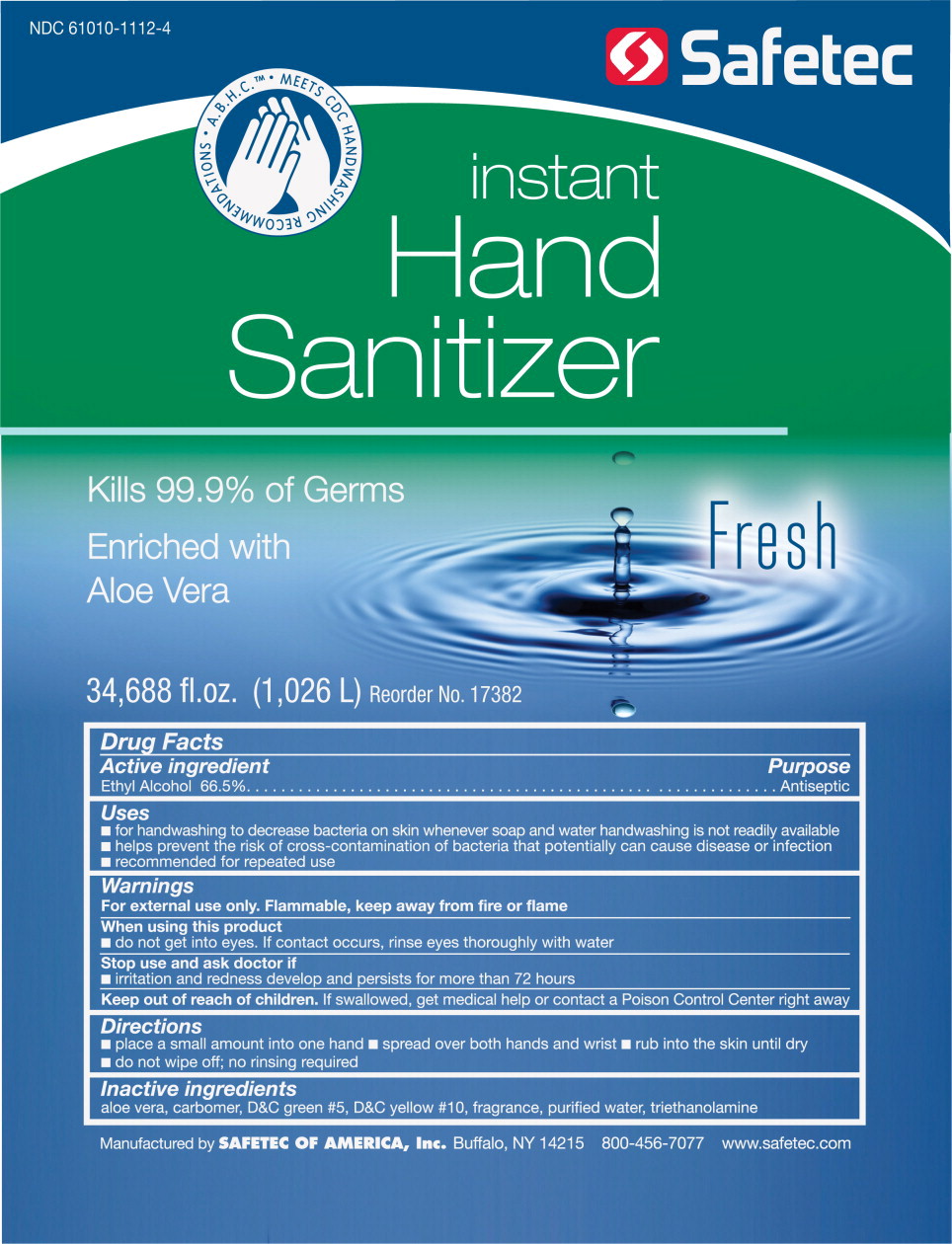 DRUG LABEL: Instant Hand Sanitizer
NDC: 61010-1112 | Form: GEL
Manufacturer: Safetec of America
Category: otc | Type: HUMAN OTC DRUG LABEL
Date: 20260116

ACTIVE INGREDIENTS: ALCOHOL 665 mL/1 L
INACTIVE INGREDIENTS: ALOE; WATER; TROLAMINE

Safetec Instant Hand Sanitizer

Drug Facts

Active Ingredient

Ethyl Alcohol 66.5%

Purpose

Antiseptic

Uses

- for handwashing to decrease bacteria on skin whenever soap and water handwashing is not readily available
- helps prevent the risk of cross-contamination of bacteria that potentially can cause disease or infection
- recommended for repeated use

Warnings

For external use only. Flammable, keep away from fire or flame

When using this product

- do not get into eyes. If contact occurs, rinse eyes thoroughly with water

Stop use and ask doctor if

- irritation and redness develop and persists for more than 72 hours

Keep out of reach of children.If swallowed, get medical help or contact a Poison Control Center right away

Directions

- place a small amount into one hand
- spread over both hands and wrist
- rub into the skin until dry
- do not wipe off; no rinsing required

Inactive ingredients

Aloe vera, carbomer, D&C green #5, D&C yellow#10, fragrance, purified water, triethanolamine

Manufactured by SAFETEC OF AMERICA, Inc.Buffalo, NY 14215 800-456-7077 www.safetec.com

PRINCIPAL DISPLAY PANEL – 34,688 fl. oz. Container Label

NDC 61010-1112-4

Safetec

instant

Hand

Sanitizer

Kills 99.9% of Germs

Enriched with

Aloe Vera

Fresh

34,688 fl.oz. (1,026 L) Reorder No. 17382